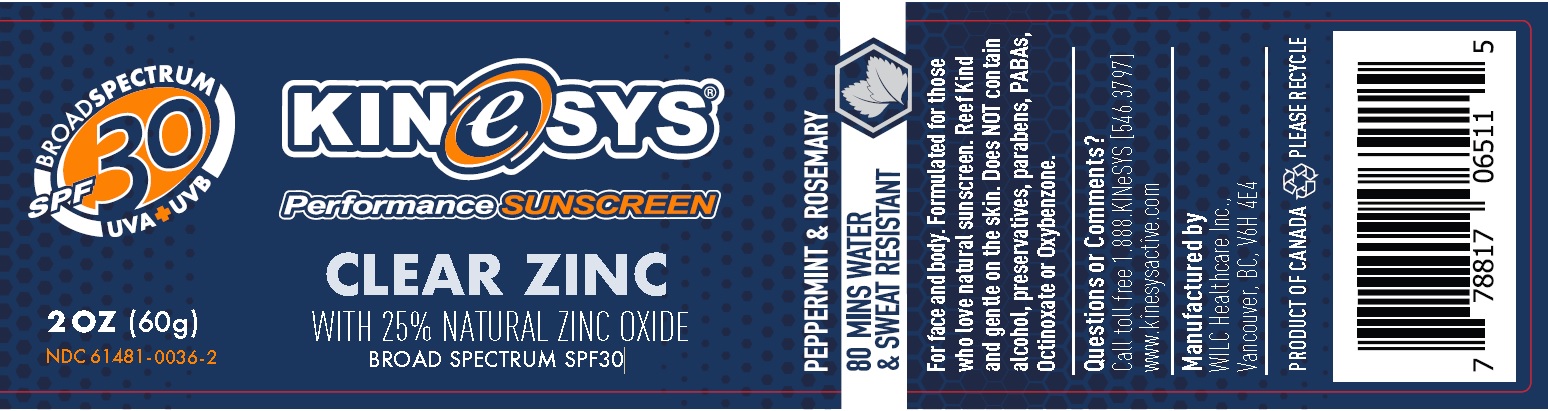 DRUG LABEL: Kinesys
NDC: 61481-0036 | Form: CREAM
Manufacturer: Wilc Healthcare Inc
Category: otc | Type: HUMAN OTC DRUG LABEL
Date: 20251010

ACTIVE INGREDIENTS: ZINC OXIDE 25 g/100 g
INACTIVE INGREDIENTS: ALOE VERA LEAF; LEVOMENOL; COCONUT OIL; PEPPERMINT OIL; ISOSTEARIC ACID; ROSEMARY OIL; SUNFLOWER OIL; TOCOPHEROL

KINeSYS Performance Sunscreen CLEAR ZINC

Active Ingredient

Zinc Oxide 25% w/w

Purpose

Sunscreen

Uses

- helps prevent sunburn
- if used as directed with other sun protection measures (see Directions), decreases the risk of skin cancer and early skin aging caused by the sun

Warnings

For external use only

Do not use

- on damaged or broken skin

When using this product

- keep out of eyes. Rinse with water to remove.

Stop use and ask a doctor

- if rash occurs

Keep out of reach of children.

If product is swallowed, get medical help or contact a Poison Control Center right away.

Directions

- Apply generously and spread evenly to all exposed skin 20 minutes before sun exposure

Reapply:

- after 80 minutes of swimming or sweating
- immediately after towel drying
- at least every 2 hours

Sun Protection Measures. Spending time in the sun increases your risk of skin cancer and early skin aging. To decrease this risk, regularly use a sunscreen with a broad spectrum SPF of 15 or higher and other sun protection measures including:

- limit time in the sun, especially from 10 a.m. – 2 p.m.
- wear long-sleeve shirts, pants, hats, and sunglasses

children under 6 months:Ask a doctor

Inactive Ingredients

Aloe Barbadensis Lead Extract, Bisabolol, Beeswax, Capric/Caprylic Triglyceride, Coconut Oil, Peppermint Oil, Polyhydroxystearic acid and Isostearic acid, Rosemary Leaf Oil, Sunflower seed oil, Tocopherols.

Other Information

- protect the product in this container from excessive heat and direct sun.

Questions or Comments?

Call toll free 1.888.KINeSYS [546.3797] www.kinesysactive.com

PRINCIPAL DISPLAY PANEL

NDC 61481-0036-2

KINeSYS Performance SUNSCREEN

CLEAR ZINC WITH 25% NATURAL ZINC OXIDE

BROAD SPECTRUM SPF 30

UVA+UVB

PEPPERMINT AND ROSEMARY

80 MINS WATER AND SWEAT RESISTANT

2 OZ (60 g)